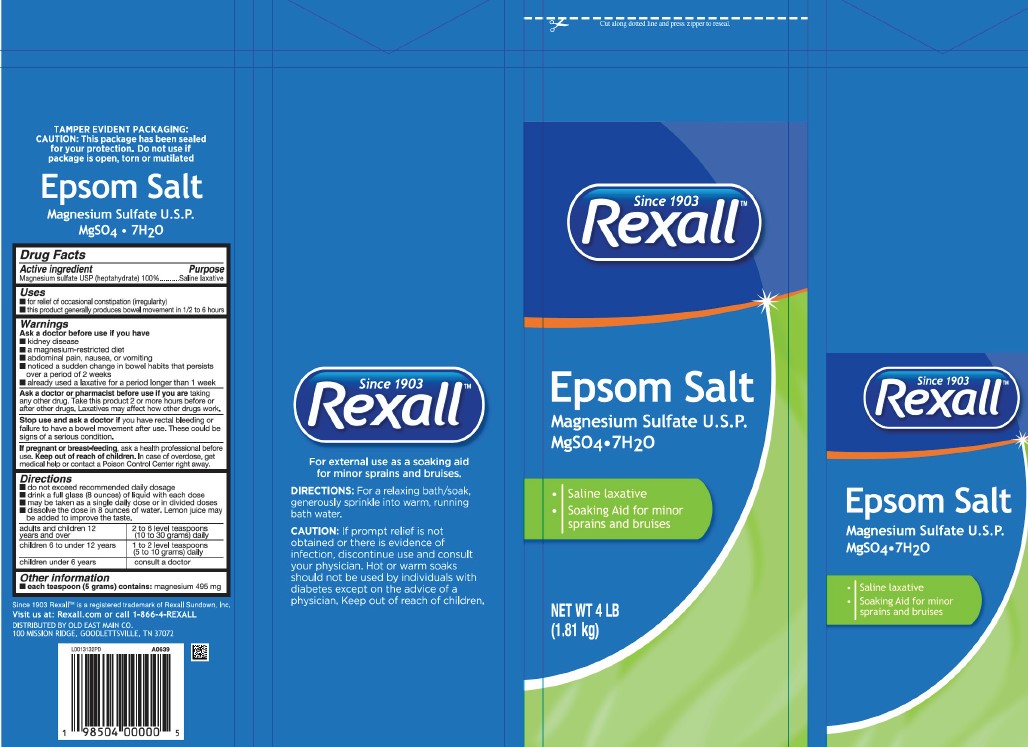 DRUG LABEL: Epsom Salt
NDC: 55910-038 | Form: GRANULE, FOR SOLUTION
Manufacturer: Old East Main Co.
Category: otc | Type: HUMAN OTC DRUG LABEL
Date: 20260302

ACTIVE INGREDIENTS: MAGNESIUM SULFATE HEPTAHYDRATE 1 g/1 g

Rexall 602.002/602AA
Epsom Salt

Tamper evident statement

TAMPER EVIDENT PACKAGING:

Caution: This package has been sealed for your protection. Do not use if package is open, torn or mutilated

Claims

Epsom Salt

Magnesium Sulfate U.S.P.

MgSO4 • 7H20

Active ingredient

Magnesium sulfate USP (heptahydrate) 100%

Purpose

Saline Laxative

Uses

- for relief of occasional constipation (irregularity)
- for this product generally produces bowel movement in 1/2 to 6 hours

Warnings

for this product

Ask a doctor before use if you have

- kidney disease
- a magnesium-restricted diet
- abdominal pain, nausea, or vomiting
- noticed a sudden change in bowel habits that persists over a period of 2 weeks
- already used a laxative for a period longer than 1 week

Ask a doctor or pharmacist before use if you are

taking any other drug. Take this product 2 or more hours before or after other drugs. Laxatives may affect how other drugs work.

Stop use and ask a doctor if

you have rectal bleeding or failure to have a bowel movement after use. These could be signs of a serious condition.

If pregnant or breast-feeding,

ask a health professional before use.

Keep out of reach of children.

In case of overdose, get medical help or contact a Poison Control Center right away.

Directions

- do not exceed recommended daily dosage
- drink a full glass (8 ounces) of liquid with each dose
- may be taken as a single daily dose or in divided doses
- dissolve the dose in 8 ounces of water. Lemon juice may be added to improve the taste.

adults and children 12 years and over - 2 to 6 level teaspoons (10 to 30 grams) daily

children 6 to under 12 years - 1 to 2 level teaspoons (5 to 10 grams) daily

children under 6 years - consult a doctor

Inactive Ingredients

None

Other information

- each teaspoon (5 grams) contains: magnesium 495 mg

Side panels disclaimers

For external use as a soaking aid for minor sprains and bruises.

DIRECTIONS: For relaxing bath/soak, generously sprinkle into warm, running bath water.

Caution: If prompt relief is not obtained or there is evidence of infection, discontinue use and consult your physician. Hot or warm soaks should not be used by individuals with diabetes except on the advice of a physician. Keep out of reach of children.

Since 1903

Rexall™

Epsom Salt

Magnesium Sulfate U.S.P.

MgSO4• 7H20

- Saline laxative
- Soaking Aid for minor sprains and bruises

Back panel disclaimer

Since 1903 Rexall is a registered trademark of Rexall Sundown, Inc.

Advere reaction

Visit us at: Rexall.com or call 1-866-4-REXALL

DISTRIBUTED BY OLD EAST MAIN CO.

100 MISSION RIDGE, GOODLETTSVILLE, TN 37072

principal panel display

Cut along dotted line and press zipper to reseal.

Since 1903

Rexall™

Epsom Salt

Magnesium Sulfate U.S.P.

MgSO4 • 7H2O

- Saline Laxative
- Soaking Aid for minor sprains and bruises

NET WT 4 LB (1.81 kg)